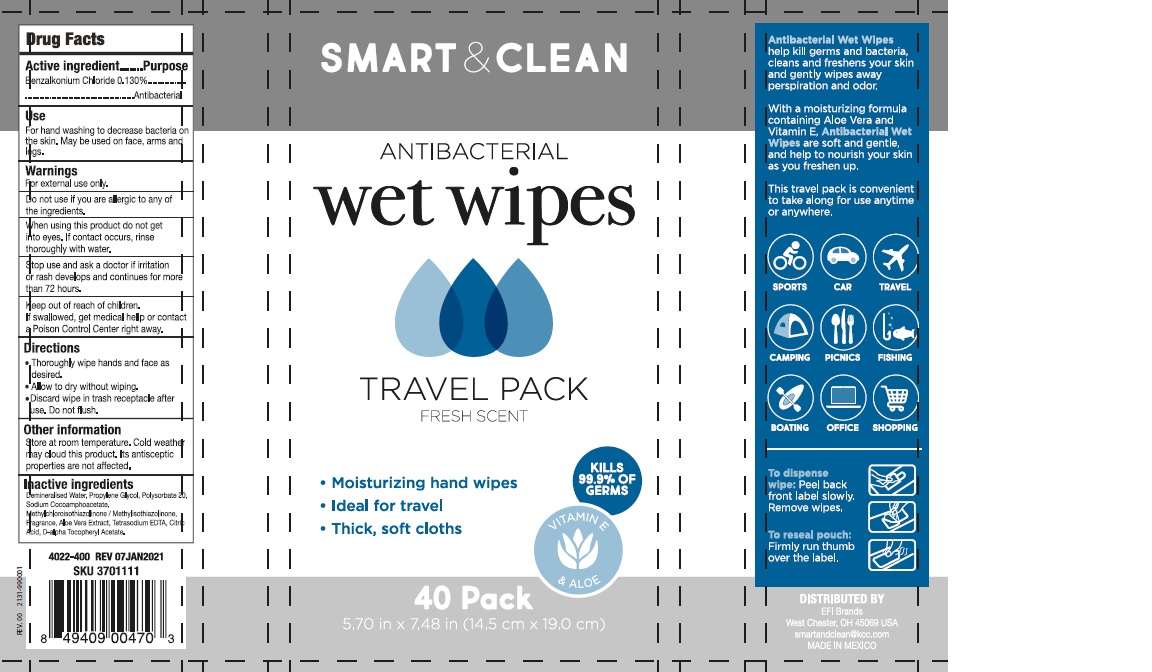 DRUG LABEL: SMART AND CLEAN
NDC: 70697-806 | Form: CLOTH
Manufacturer: INDELPA, S.A DE C.V
Category: otc | Type: HUMAN OTC DRUG LABEL
Date: 20230110

ACTIVE INGREDIENTS: BENZALKONIUM CHLORIDE 0.13 g/100 g
INACTIVE INGREDIENTS: PROPYLENE GLYCOL 0.5 g/100 g; ALOE VERA LEAF 0.05 g/100 g; CITRIC ACID MONOHYDRATE 0.018 g/100 g; METHYLCHLOROISOTHIAZOLINONE/METHYLISOTHIAZOLINONE MIXTURE 0.1 g/100 g; .ALPHA.-TOCOPHEROL ACETATE, DL- 0.01 g/100 g; METHYLCHLOROISOTHIAZOLINONE 0.1 g/100 g; SODIUM COCOAMPHOACETATE 0.2 g/100 g; POLYSORBATE 20 0.3 g/100 g; EDETATE SODIUM 0.03 g/100 g; WATER 98.562 g/100 g

ACTIVE INGREDIENT

Benzalkonium Chloride 0.130%

PURPOSE

Antibacterial

INDICATIONS AND USAGE

For hand washing to decrease bacteria on
the skin. May be used on face, arms and
legs.

WARNINGS

For external use only

DO NOT USE

if you are allergic to any of the ingredients

WHEN USING

this product do not get into eyes. If contact occurs, rinse thoroughly with water.

STOP USE

if irritation or rash develops and continues for more than 72 hours.

ASK DOCTOR

if irritation or rash develops and continues for more than 72 hours.

KEEP OUT OF REACH OF CHILDREN

If swallowed, get medical hellp or contact a Poison Control Center right away.

INSTRUCTIONS FOR USE

- Thoroughly wipe hands and face as

desired.

- Allow to dry without wiping.
- Discard wipe in trash receptacle after
  use. Do not flush.

STORAGE AND HANDLING

Store at room temperature. Cold weather
may cloud this product. Its antisceptic
properties are not affected.

INACTIVE INGREDIENT

Water, Propylene Glycol, Polysorbate 20,
Sodium Cocoamphoacetate,Fragrance,
Methylchloroisothiazolinone, Aloe Extract,
Tetrasodium EDTA, Citric Acid, Vitamin E.

Dosage: Liquid

Administration: Topical